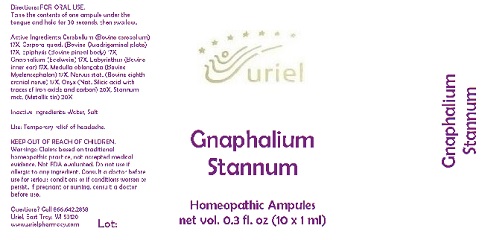 DRUG LABEL: Gnaphalium Stannum
NDC: 48951-5027 | Form: LIQUID
Manufacturer: Uriel Pharmacy Inc.
Category: homeopathic | Type: HUMAN OTC DRUG LABEL
Date: 20180521

ACTIVE INGREDIENTS: BOS TAURUS CEREBELLUM 17 [hp_X]/1 mL; BOS TAURUS BRAIN 17 [hp_X]/1 mL; BOS TAURUS PINEAL GLAND 17 [hp_X]/1 mL; PSEUDOGNAPHALIUM LUTEOALBUM LEAF 17 [hp_X]/1 mL; SUS SCROFA EAR 17 [hp_X]/1 mL; BOS TAURUS NERVE 17 [hp_X]/1 mL; BIFENTHRIN 20 [hp_X]/1 mL; TIN 20 [hp_X]/1 mL
INACTIVE INGREDIENTS: WATER; SODIUM CHLORIDE

Gnaphalium Stannum

INDICATIONS AND USAGE

Directions: FOR ORAL USE.

DOSAGE AND ADMINISTRATION

Take the contents of one ampule under the tongue and hold for 30 seconds, then swallow.

ACTIVE INGREDIENT

Active Ingredients: Cerebellum (Bovine cerebellum) 17X, Corpora quad. (Bovine Quadrigeminal plate) 17X, Epiphysis (Bovine pineal body) 17X, Gnaphalium (Edelweiss) 17X, Labyrinthus (Bovine inner ear) 17X, Medulla oblongata (Bovine Myelencephalon) 17X, Nervus stat. (Bovine eighth cranial nerve) 17X, Onyx (Nat. Silicic acid with traces of iron oxide and carbon) 20X, Stannum met. (Metallic tin) 20X

Inactive Ingredients: Water, Salt

PURPOSE

Use: Temporary relief of headache.

KEEP OUT OF REACH OF CHILDREN.

WARNINGS

Warnings: Claims based on traditional homeopathic practice, not accepted medical evidence. Not FDA evaluated. Do not use if allergic to any ingredient. Consult a doctor before use for serious conditions or if conditions worsen or persist. If pregnant or nursing, consult a doctor before use.

QUESTIONS

Questions? Call 866.642.2858 Uriel, East Troy, WI 53120 www.urielpharmacy.com